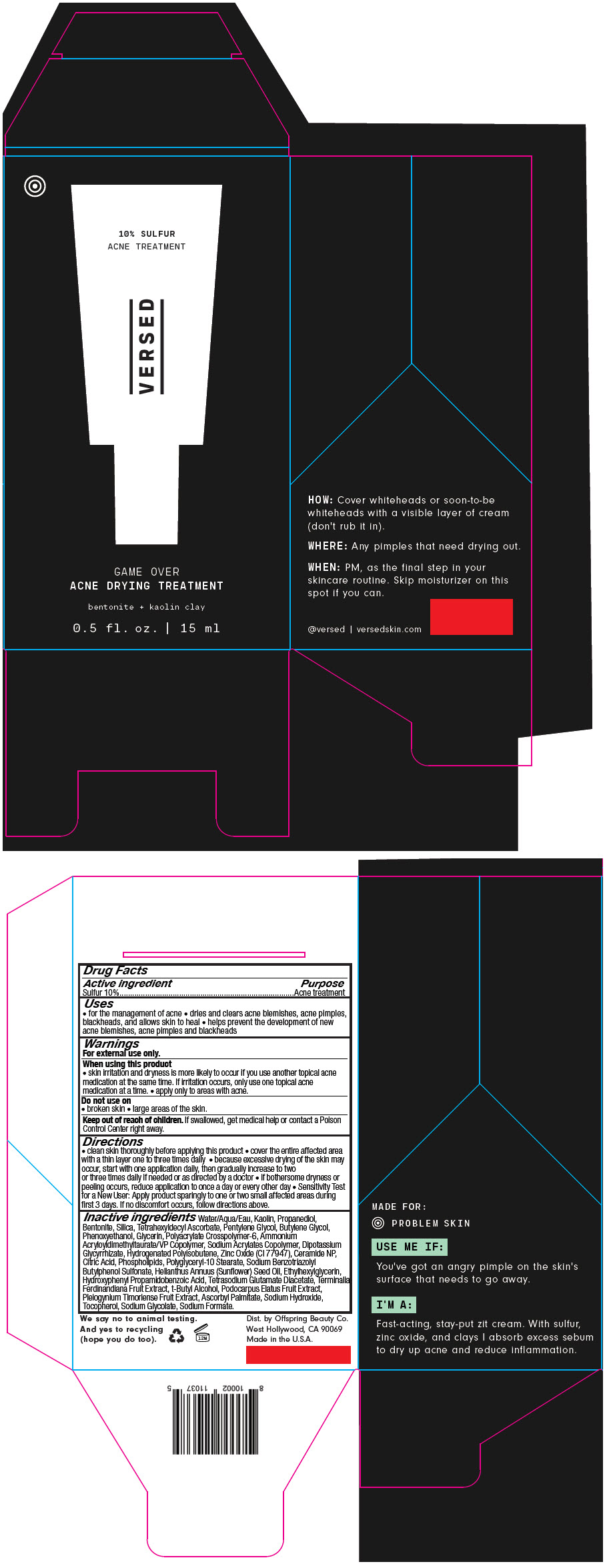 DRUG LABEL: Game Over Acne Drying Treatment
NDC: 73690-026 | Form: CREAM
Manufacturer: Offspring Beauty Co.
Category: otc | Type: HUMAN OTC DRUG LABEL
Date: 20240109

ACTIVE INGREDIENTS: Sulfur 100 mg/1 mL
INACTIVE INGREDIENTS: WATER; KAOLIN; PROPANEDIOL; BENTONITE; SILICON DIOXIDE; TETRAHEXYLDECYL ASCORBATE; PENTYLENE GLYCOL; BUTYLENE GLYCOL; PHENOXYETHANOL; GLYCERIN; AMMONIUM ACRYLOYLDIMETHYLTAURATE, DIMETHYLACRYLAMIDE, LAURYL METHACRYLATE AND LAURETH-4 METHACRYLATE COPOLYMER, TRIMETHYLOLPROPANE TRIACRYLATE CROSSLINKED (45000 MPA.S); AMMONIUM ACRYLOYLDIMETHYLTAURATE/VP COPOLYMER; SODIUM ACRYLATE/SODIUM ACRYLOYLDIMETHYLTAURATE COPOLYMER (4000000 MW); GLYCYRRHIZINATE DIPOTASSIUM; HYDROGENATED POLYBUTENE (1300 MW); CERAMIDE NP; CITRIC ACID MONOHYDRATE; LECITHIN, SOYBEAN; POLYGLYCERYL-10 STEARATE; SODIUM BENZOTRIAZOLYL BUTYLPHENOL SULFONATE; SUNFLOWER OIL; ETHYLHEXYLGLYCERIN; HYDROXYPHENYL PROPAMIDOBENZOIC ACID; TETRASODIUM GLUTAMATE DIACETATE; KAKADU PLUM; PODOCARPUS ELATUS FRUIT; PLEIOGYNIUM TIMORIENSE FRUIT; ZINC OXIDE; TERT-BUTYL ALCOHOL; ASCORBYL PALMITATE; SODIUM HYDROXIDE; TOCOPHEROL; SODIUM GLYCOLATE; SODIUM FORMATE

Game Over Acne Drying Treatment

Drug Facts

Active ingredient

Sulfur 10%

Purpose

Acne treatment

Uses

- for the management of acne
- dries and clears acne blemishes, acne pimples, blackheads, and allows skin to heal
- helps prevent the development of new acne blemishes, acne pimples and blackheads

Warnings

For external use only.

When using this product

- skin irritation and dryness is more likely to occur if you use another topical acne medication at the same time. If irritation occurs, only use one topical acne medication at a time.
- apply only to areas with acne.

Do not use on

- broken skin
- large areas of the skin.

Keep out of reach of children. If swallowed, get medical help or contact a Poison Control Center right away.

Directions

- clean skin thoroughly before applying this product
- cover the entire affected area with a thin layer one to three times daily
- because excessive drying of the skin may occur, start with one application daily, then gradually increase to two or three times daily if needed or as directed by a doctor
- if bothersome dryness or peeling occurs, reduce application to once a day or every other day
- Sensitivity Test for a New User: Apply product sparingly to one or two small affected areas during first 3 days. If no discomfort occurs, follow directions above.

Inactive ingredients

Water/Aqua/Eau, Kaolin, Propanediol, Bentonite, Silica, Tetrahexyldecyl Ascorbate, Pentylene Glycol, Butylene Glycol, Phenoxyethanol, Glycerin, Polyacrylate Crosspolymer-6, Ammonium Acryloyldimethyltaurate/VP Copolymer, Sodium Acrylates Copolymer, Dipotassium Glycyrrhizate, Hydrogenated Polyisobutene, Zinc Oxide (CI 77947), Ceramide NP, Citric Acid, Phospholipids, Polyglyceryl-10 Stearate, Sodium Benzotriazolyl Butylphenol Sulfonate, Helianthus Annuus (Sunflower) Seed Oil, Ethylhexylglycerin, Hydroxyphenyl Propamidobenzoic Acid, Tetrasodium Glutamate Diacetate, Terminalia Ferdinandiana Fruit Extract, t-Butyl Alcohol, Podocarpus Elatus Fruit Extract, Pleiogynium Timoriense Fruit Extract, Ascorbyl Palmitate, Sodium Hydroxide, Tocopherol, Sodium Glycolate, Sodium Formate.

Dist. by Offspring Beauty Co.
West Hollywood, CA 90069

PRINCIPAL DISPLAY PANEL - 15 ml Tube Carton

10% SULFUR
ACNE TREATMENT

VERSED

GAME OVER
ACNE DRYING TREATMENT

bentonite + kaolin clay

0.5 fl. oz. | 15 ml